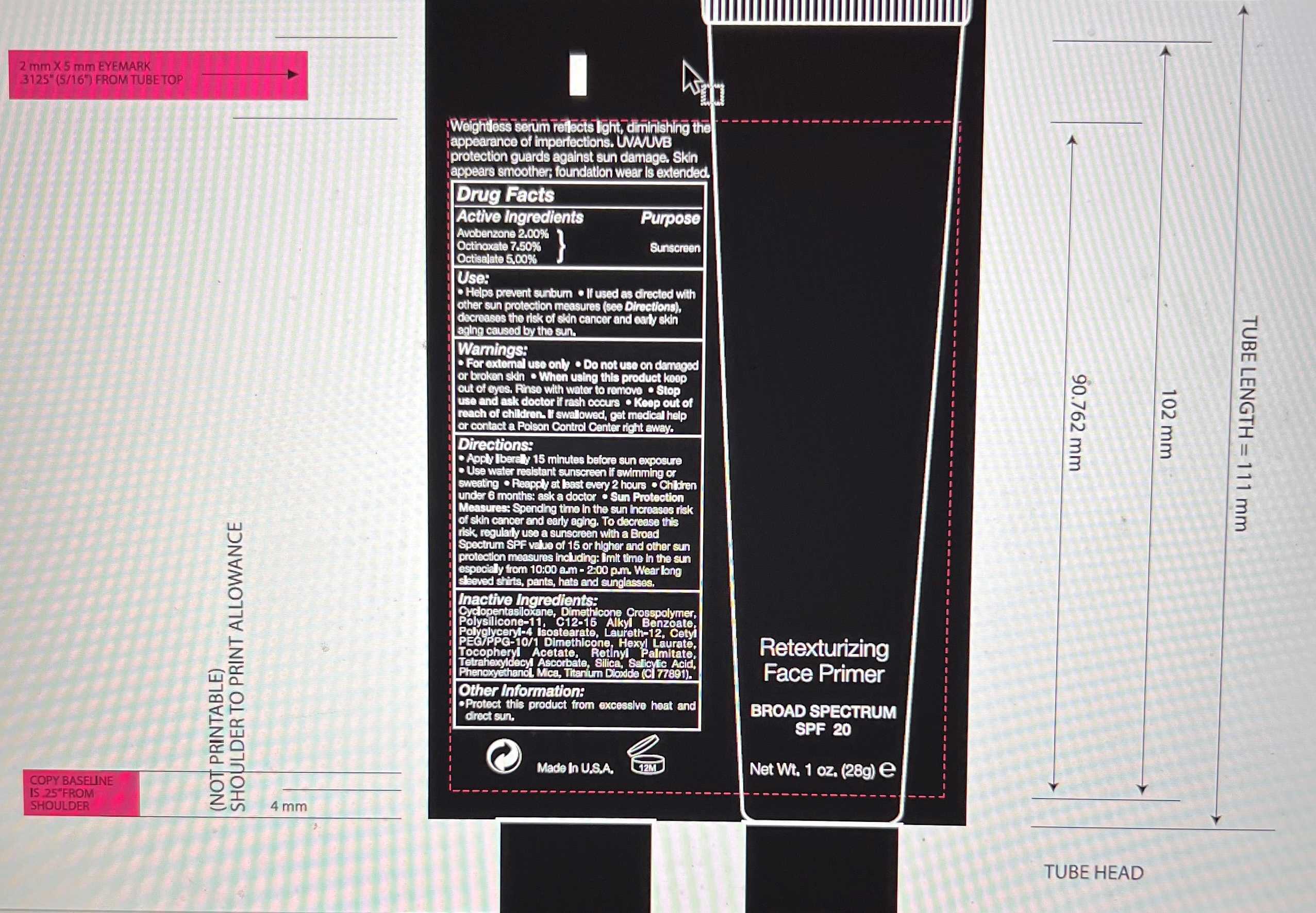 DRUG LABEL: RETEXTURIZING PRIMER BROAD SPECTRUM SPF 20
NDC: 59735-800 | Form: CREAM
Manufacturer: MANA PRODUCTS,INC.
Category: otc | Type: HUMAN OTC DRUG LABEL
Date: 20250328

ACTIVE INGREDIENTS: AVOBENZONE 2 g/100 g; OCTINOXATE 7.5 g/100 g; OCTISALATE 5 g/100 g
INACTIVE INGREDIENTS: DIMETHICONE/VINYL DIMETHICONE CROSSPOLYMER (SOFT PARTICLE); ALKYL (C12-15) BENZOATE; DIMETHICONE CROSSPOLYMER (450000 MPA.S AT 12% IN CYCLOPENTASILOXANE); CETYL PEG/PPG-10/1 DIMETHICONE (HLB 5); TETRAHEXYLDECYL ASCORBATE; .ALPHA.-TOCOPHEROL ACETATE; CYCLOMETHICONE; PHENOXYETHANOL; POLYGLYCERYL-4 ISOSTEARATE; HEXYL LAURATE; LAURETH-12; VITAMIN A PALMITATE; SALICYLIC ACID; MICA; SILICON DIOXIDE; TITANIUM DIOXIDE

RETEXTURIZING PRIMER BROAD SPECTRUM SPF 20

ACTIVE INGREDIENTS

Avobenzone 2%

Octinoxate 7.5%

Octisalate 5%

USES

Helps prevent sunburn.
If used as directed with other sun protection measures (see Directions), decreases the risk of skin cancer and early skin aging caused by the sun.

WARNINGS

- For external use only.
- Do not use on damaged or broken skin.
- When using this product keep out of eyes. Rinse with water to remove.

DIRECTIONS

- Apply liberally 15 minutes before sun exposure.
- Reapply at least every 2 hours.
- Use a water-resistant sunscreen if swimming or sweating.
- Sun Protection Measures:
- Spending time in the sun increases risk of skin cancer and early aging. To decrease this risk, regularly use a sunscreen with a Broad-Spectrum SPF value of 15 or higher and other sun protection measures including:

limit time in the sun especially from 10:00 a.m. - 2:00 p.m.

- wear long sleeved shirts, pants, hats and sunglasses.
- Children under 6 months of age: ask a doctor.

OTHER INFORMATION

Protect the product in this container from excessive heat and direct sun.

INACTIVE INGREDIENTS

Cyclopentasiloxane, Dimethicone Crosspolymer, Polysilicone-11, C12-15 Alkyl Benzoate, Polyglyceryl-4 Isostearate, Cetyl PEG/PPG-10/1 Dimethicone, Hexyl Laurate, Laureth-12, Tetrahexyldecyl Ascorbate, Tocopheryl Acetate, Retinyl Palmitate, Salicylic Acid, Mica, Silica, Phenoxyethanol, Titanium Dioxide

Stop use and ask a doctor if rash occurs.

RECENT MAJOR CHANGES

dosage & admin update

Keep out of reach of children. If product is swallowed, get medical help or contact a Poison Control Center right away.